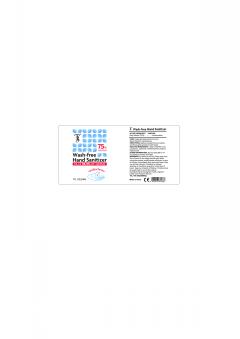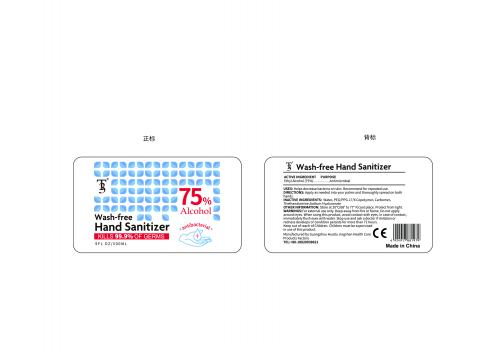 DRUG LABEL: not have
NDC: 74996-012 | Form: SPRAY
Manufacturer: Guangzhou huadu jingshen health care products factory
Category: otc | Type: HUMAN OTC DRUG LABEL
Date: 20200505

ACTIVE INGREDIENTS: ALCOHOL 75 mL/100 mL
INACTIVE INGREDIENTS: HYALURONATE SODIUM; PEG/PPG-17/6 COPOLYMER; WATER; CARBOMER HOMOPOLYMER, UNSPECIFIED TYPE; TROLAMINE

Wash-free Hand Sanitizer

ACTIVE INGREDIENT

Ethyl Alcohol(75%)

PURPOSE

Antimicrobial

USES

Helps decrease bacteria on skin.Recommend for repeated use.

WARNINGS

For external use only.Keep away from fire or flame.Do not apply around eyes.When using this product,avoid contact with eyes.In case of contact, immediately flush eyes with water.Stop use and ask a doctor if imitaton or redness develops or condition persists for more than 72 hours.Keep out of reach of Children.Children must be supervised in use of this product.

DIRECTIONS

Apply as needed into your palms and thoroughly spread on both hands.

OTHER INFORMATION

Store at 20°C(68°to77°F) cool place.Protect from light.

INACTIVE INGREDIENTS

Water,PEG/PPG-17/ 6 Copolymer,Carbomer, Triethanolamine,Sodium Hyaluronate